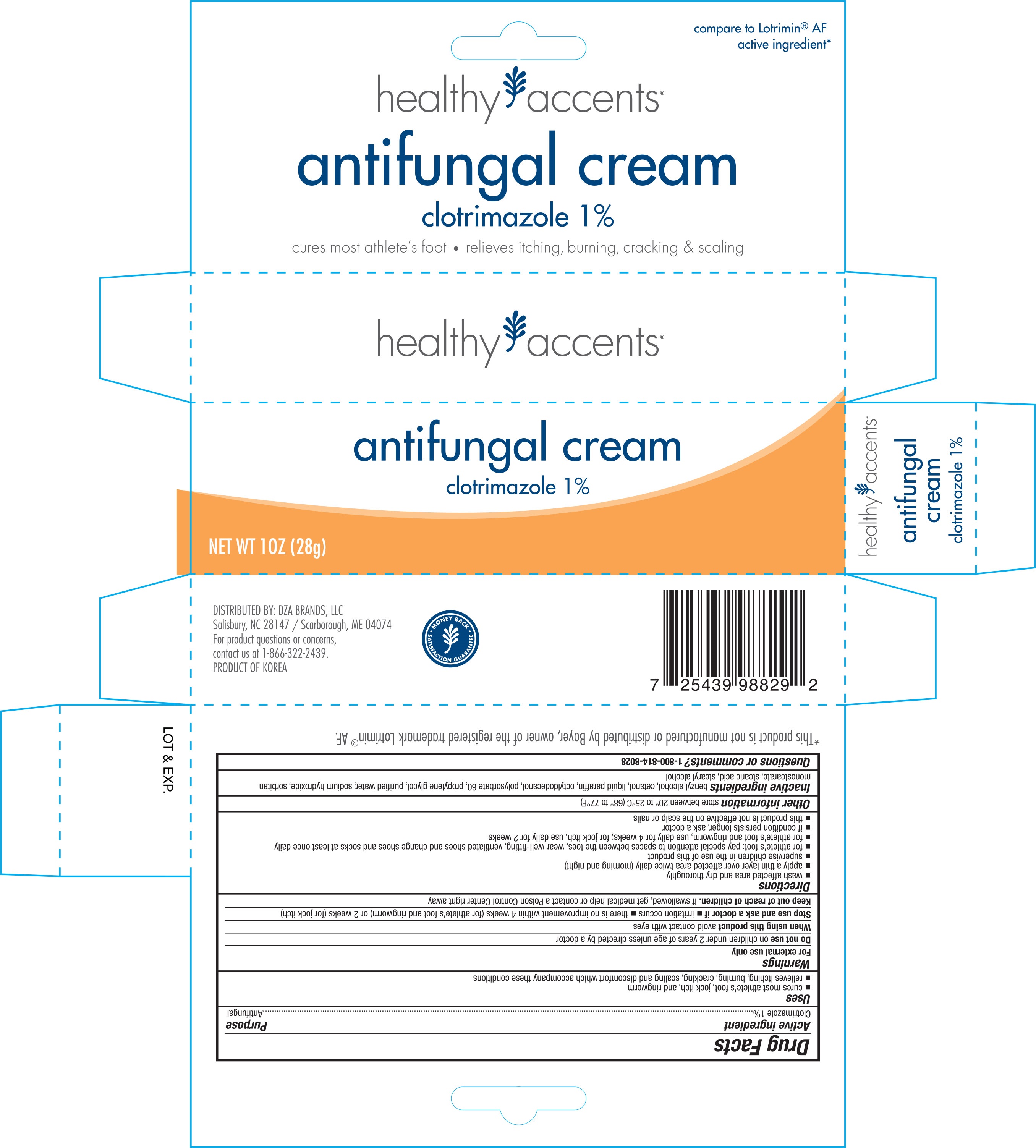 DRUG LABEL: Healthy Accents Antifungal
NDC: 55316-829 | Form: CREAM
Manufacturer: DZA Brands LLC
Category: otc | Type: HUMAN OTC DRUG LABEL
Date: 20160803

ACTIVE INGREDIENTS: CLOTRIMAZOLE 10 g/1 g
INACTIVE INGREDIENTS: BENZYL ALCOHOL; CETYL ALCOHOL; PARAFFIN; OCTYLDODECANOL; POLYSORBATE 60; PROPYLENE GLYCOL; WATER; SODIUM HYDROXIDE; SORBITAN MONOSTEARATE; STEARIC ACID; STEARYL ALCOHOL

Active ingredient Purpose

Clotrimazole 1%...............................................................Antifungal

Uses

- cures most athlete's foot, jock itch, and ringworm
- relieves itching, burning, cracking, scaling, and discomfort which accompany these conditions

Warnings

For external use only

Do not use on children under 2 years of age unless directed by a doctor

When using this product avoid contact with eyes

Stop use and ask a doctor if

- irritation occurs
- there is no improvement within 4 weeks (for athlete's foot and ringworm) or 2 weeks (for jock itch)

Keep out of reach of children. If swallowed, get medical help or contact a Poison Control Center right away

Directions

- wash affected area and dry thoroughly
- apply a thin layer over affected area twice daily (morning and night)
- supervise children in the use of this product
- for athlete's foot: pay special attention to spaces between the toes, wear well-fitting, ventilated shoes and chagne shoes and socks at least once daily
- for athlete's foot and ringworm, use daily for 4 weeks; for jock itch, use daily for 2 weeks
- if condtion persists longer, ask a doctor
- this product is not effectiveo n the scalp or nails

Other information store between 20° to 25° (68° to 77°F)

Inactive ingredients

benzyl alcohol, cetanol, liquid paraffin, octyldodecanol, polysorbate 60, propylene glycol, purified water, sodium hydroxide, sorbitan monostearate, stearic acid, stearyl alcohol

DOSAGE AND ADMINISTRATION

Distributed by:

Salisbury, NC 28147

Scarborough, ME 04074

Product of Korea